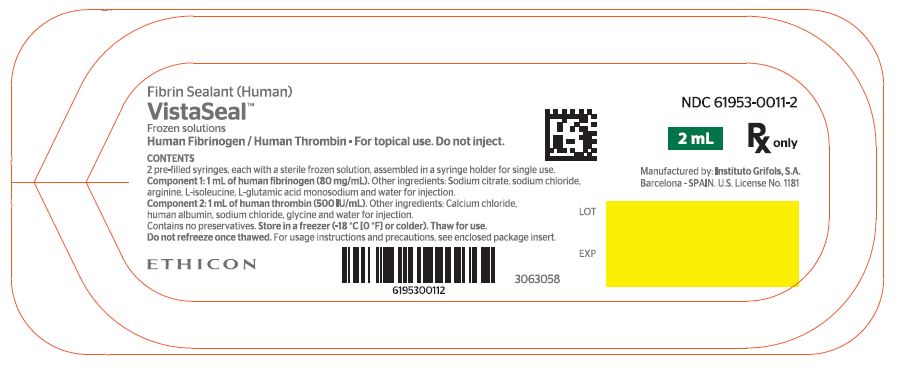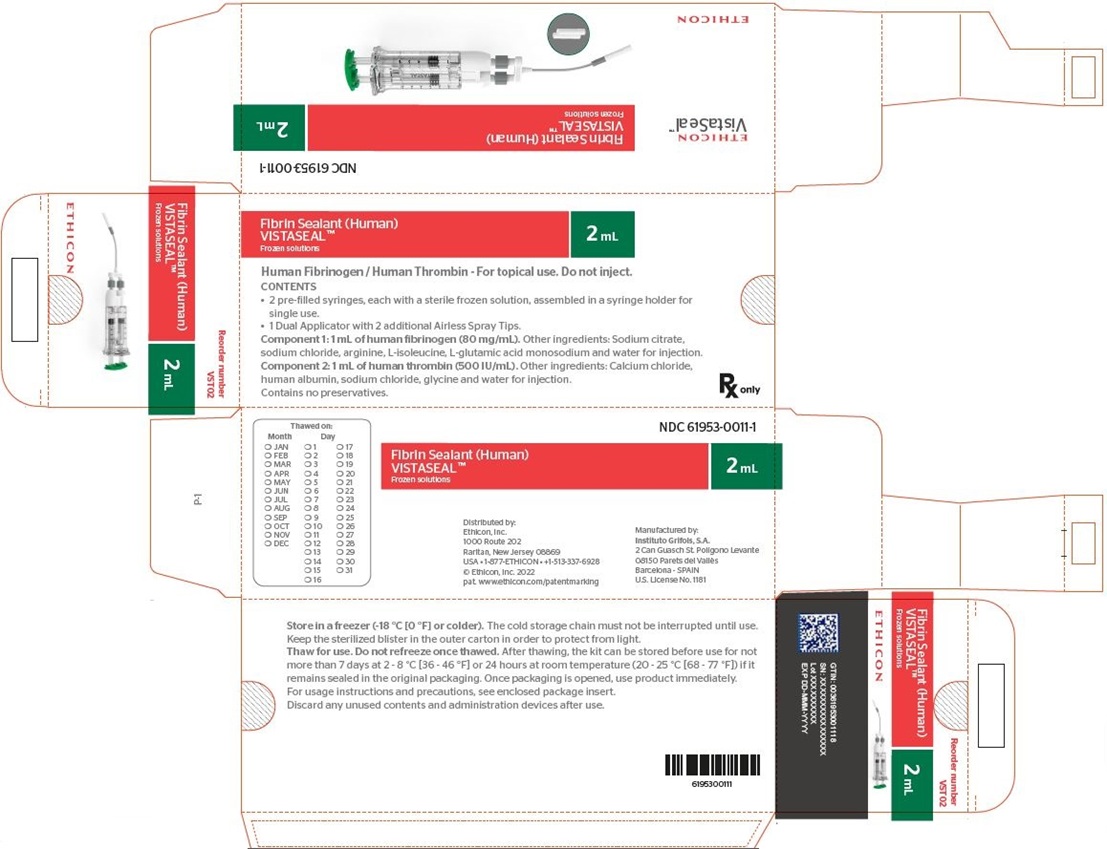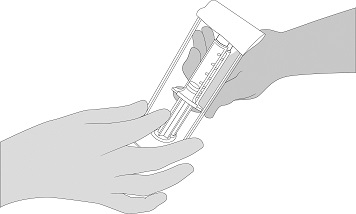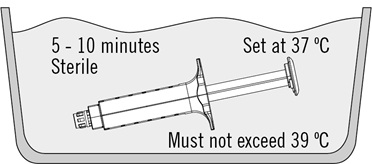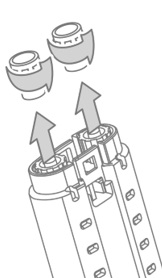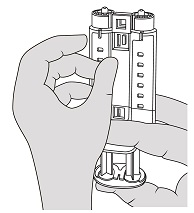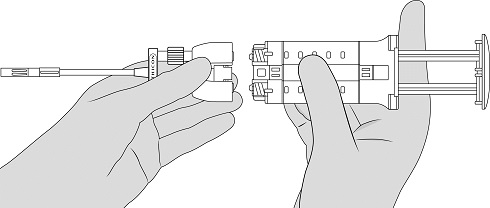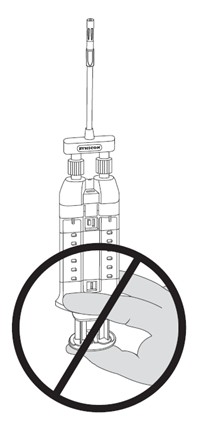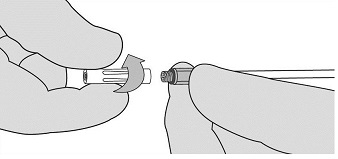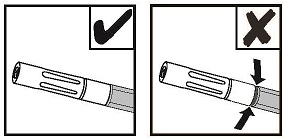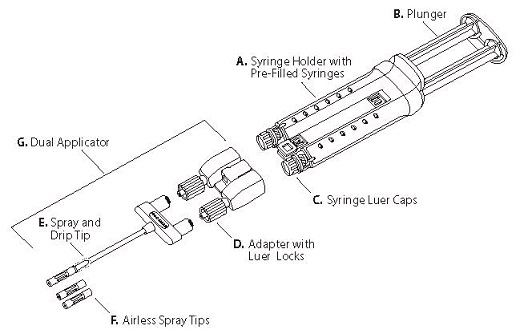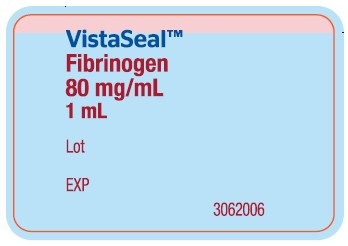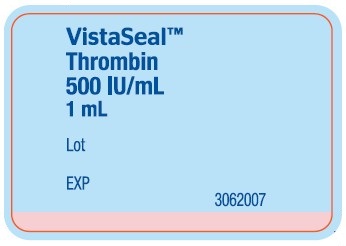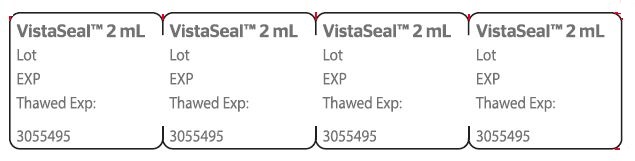 DRUG LABEL: VISTASEAL
NDC: 61953-0011 | Form: KIT | Route: TOPICAL
Manufacturer: GRIFOLS USA, LLC
Category: other | Type: PLASMA DERIVATIVE
Date: 20250813

ACTIVE INGREDIENTS: Fibrinogen Human 80 mg/1 mL; Thrombin Human 500 [iU]/1 mL
INACTIVE INGREDIENTS: Sodium Citrate, Unspecified Form; Sodium Chloride; Arginine; Isoleucine; Monosodium Glutamate Anhydrous; Water; Calcium Chloride; Albumin Human; Sodium Chloride; Glycine; Water

HIGHLIGHTS OF PRESCRIBING INFORMATION

These highlights do not include all the information needed to use VISTASEAL™ safely and effectively. See full prescribing information for VISTASEAL.
VISTASEAL™ [Fibrin Sealant (Human)]
Frozen solutions of fibrinogen and thrombin
For Topical Use Only
Initial U.S. Approval: 2017

1 INDICATIONS AND USAGE

VISTASEAL™, a fibrin sealant, is indicated as an adjunct to hemostasis for mild to moderate bleeding in patients undergoing surgery when control of bleeding by standard surgical techniques (such as suture, ligature, and cautery) is ineffective or impractical. VISTASEAL is effective in heparinized patients. (1)

RECENT MAJOR CHANGES

Indications and Usage (1) | 9/2024
Dosage and Administration (2) | 9/2024

2 DOSAGE AND ADMINISTRATION

For topical use only.

- The recommended dose of VISTASEAL is based on the surface area coverage as described in Section 2.1 Table 1.
- After thawing, use VISTASEAL within 7 days if stored at 2 ºC - 8 ºC [36 ºF - 46 ºF], or within 24 hours if stored at room temperature (20 °C ‑ 25 °C [68 ºF - 77 ºF]), if it remains sealed in the original packaging. (2.2,16)
- Prior to applying VISTASEAL, use standard techniques (e.g., intermittent application of compresses, swabs, use of suction devices) to dry the surface area of the target bleeding site. (2.3)
- Apply VISTASEAL by dripping or spraying. When applying VISTASEAL using a spray device, ensure that the distance from the tissue is within the recommended ranges for the applicator tip used. (2.3, 2.4)
- Apply a sufficient volume of VISTASEAL to entirely cover the intended application area with a thin layer. (2.1, 2.4)

3 DOSAGE FORMS AND STRENGTHS

VISTASEAL is supplied as a kit consisting of two separate packages:

- A package containing one syringe each of human fibrinogen 80 mg/mL (component 1) and human thrombin 500 IU/mL (component 2) sterile frozen solutions which are assembled in a syringe holder. (3)
- A package containing a VISTASEAL Dual Applicator with two additional Airless Spray Tips. (3)

VISTASEAL is available in the following package sizes:

Package size (Total volume) | Human fibrinogen | Human thrombin
2 mL | 1 mL | 1 mL
4 mL | 2 mL | 2 mL
6 mL | 3 mL | 3 mL
10 mL | 5 mL | 5 mL

4 CONTRAINDICATIONS

- Do not inject directly into the circulatory system. (4)
- Do not use for the treatment of severe or brisk arterial bleeding. (4)
- Do not use in patients with history of anaphylaxis or severe systemic reactions to human blood products. (4)
- Do not use VISTASEAL for spraying unless the minimum recommended distance from the applicator tip to the bleeding site can be achieved. (4)

5 WARNINGS AND PRECAUTIONS

- Thromboembolic events may occur if VISTASEAL is administered intravascularly. (5.1)
- Hypersensitivity reactions can occur. (5.2)
- May carry a risk of transmitting infectious agents, e.g., viruses, the variant Creutzfeldt-Jakob disease (vCJD) agent and, theoretically, the Creutzfeldt-Jakob disease (CJD) agent. (5.3)

6 ADVERSE REACTIONS

The most common adverse reactions (reported in >1% of patients) were procedural pain, and nausea. (6)

To report SUSPECTED ADVERSE REACTIONS, contact Grifols Therapeutics LLC at 1-800-520-2807 or FDA at 1-800-FDA-1088 or http://www.fda.gov/medwatch.

FULL PRESCRIBING INFORMATION

1 INDICATIONS AND USAGE

VISTASEAL, a fibrin sealant (human), is indicated as an adjunct to hemostasis for mild to moderate bleeding in patients undergoing surgery when control of bleeding by standard surgical techniques (such as suture, ligature, and cautery) is ineffective or impractical. VISTASEAL is effective in heparinized patients.

2 DOSAGE AND ADMINISTRATION

For topical use only.

2.1 Dosage

The recommended dose of VISTASEAL is based on the surface area coverage.

The approximate surface area coverage for each VISTASEAL package size is provided in Table 1.

Table 1. Surface Area Coverage
VISTASEAL package size | Surface area coverage (cm^2) Application by dripping or spray (1 mm thick layer)
2 mL | 16 - 22
4 mL | 32 - 44
6 mL | 48 - 66
10 mL | 80 - 110

Dose depends on variables including, but not limited to, the type of surgical intervention, the size of the area, the intended application method, and the number of applications.

Apply a sufficient volume of VISTASEAL to entirely cover the intended application area with a thin layer. Repeat the application if necessary.

2.2 Preparation and Handling

Prepare and administer the product only according to the instructions and with the recommended devices.

An overview of thawing methods and storage after thawing is provided in Table 2.

Table 2. Thawing and storage after thawing
Thawing method | Thawing time per package size |  | Maximum storage time after thawing
Thawing method | For 2 mL and 4 mL | For 6 mL and 10 mL | Maximum storage time after thawing
Refrigerator (2 – 8 °C [36 – 46 °F]) | Minimum 7 hours | Minimum 10 hours | 7 days at 2 - 8 °C [36 – 46 °F] (refrigerator) in original package OR 24 hours at 20 - 25 °C [68 - 77 °F] (room temperature) in original package
Room Temperature (20 - 25 °C [68 – 77 °F]) | Minimum 70 minutes | Minimum 90 minutes | 7 days at 2 - 8 °C [36 – 46 °F] (refrigerator) in original package OR 24 hours at 20 - 25 °C [68 - 77 °F] (room temperature) in original package
Sterile water bath set at 37 °C [99 °F] inside sterile field. The water temperature must not exceed 39 °C [102 °F]. | Minimum 5 minutes. Do not exceed 10 minutes. | Minimum 5 minutes. Do not exceed 10 minutes. | Use immediately during the surgery

Preferred thawing methods

Option 1: Refrigerator thawing

1. Remove carton from freezer and place it unopened in the refrigerator for thawing at 2 – 8 °C [36 – 46 °F] for
  a minimum of 7 hours for the 2 mL and the 4 mL package sizes
  a minimum of 10 hours for the 6 mL and the 10 mL package sizes

After thawing, it is not necessary to warm the product for its use.
After thawing, the solutions must be clear to slightly opalescent, colorless to pale yellow and must not be cloudy nor have deposits.

Option 2: Room Temperature Thawing
Remove carton from freezer, open it and take out the two blisters.
Place the blister containing the VISTASEAL Dual Applicator at room temperature until the VISTASEAL fibrin sealant (human) is ready to use.

Thaw blister with VISTASEAL pre-filled syringes at room temperature using the following steps:

1. Place the blister containing the syringe holder with pre-filled syringes on a surface at room temperature (20 ºC - 25 ºC, [68 - 77 ºF]) for
  a minimum of 70 minutes for the 2 mL and the 4 mL package sizes
  a minimum of 90 minutes for the 6 mL and the 10 mL package sizes

After thawing, it is not necessary to warm the product for its use.
After thawing, the solutions must be clear to slightly opalescent, colorless to pale yellow and must not be cloudy nor have deposits.

Post-Thawing Storage:
After thawing, the kit containing the VISTASEAL syringe holder with pre-filled syringes and Dual Applicator can be stored before use for not more than 7 days in the refrigerator at 2 ‑ 8 ºC [36 - 46 ºF] or 24 hours at room temperature (20 - 25 °C [68 - 77 ºF]) if it remains sealed in the original packaging. Once the blisters are opened, use VISTASEAL immediately during the surgery and discard any unused contents.
Once thawed, do not refreeze.

Transferring instructions:

1. After thawing, remove the blister from the surface at room temperature or remove carton from the refrigerator at 2 - 8 °C [36 - 46 ºF] and take out the two blisters.
2. Open the blister and confirm that the VISTASEAL pre-filled syringes are completely thawed. After thawing, the solutions must be clear to slightly opalescent, colorless to pale yellow and must not be cloudy nor have deposits. Make the VISTASEAL syringe holder with pre-filled syringes available to a second person for transfer to the sterile field. The outside of the blister should not come in contact with the sterile field. See Figure 1.
  Figure 1

Sterile Water Bath (Quick Thawing) method
Remove carton from freezer, open it and take out the two blisters.
Place the blister containing the VISTASEAL Dual Applicator at room temperature until VISTASEAL fibrin sealant (human) is ready to use.
Thaw VISTASEAL pre-filled syringes inside the sterile field in a sterile thermostatic water bath set at a temperature of 37 °C [99 °F] using the following steps:
NOTE: Prepare and maintain the sterile water bath following the instructions of the water bath manufacturer and according to hospital procedures to maintain a sterile surgical field and avoid the possibility of contamination.
NOTE: Once the VISTASEAL blisters are opened, use the product immediately during surgery. Use sterile technique to avoid the possibility of contamination due to improper handling, and follow the steps below accurately. Do not remove the syringe luer cap until thawing is complete and the Dual Applicator is ready to be attached.

1. Open the blister and make the VISTASEAL syringe holder with pre-filled syringes available to a second person for transfer to the sterile field. The outside of the blister should not come in contact with the sterile field. See Figure 1.
2. Place the syringe holder with pre-filled syringes directly into the sterile water bath ensuring that it is completely immersed in the water. See Figure 2.
3. At 37 ºC, the time needed is approximately 5 minutes for the 2 mL, 4 mL, 6 mL, and 10 mL package sizes, but must not be left at this temperature for longer than 10 minutes.
  NOTE: The temperature of the water must not exceed 39°C. To monitor the water temperature, you may use a thermometer and change the water as necessary.
4. Dry the syringe holder with pre-filled syringes after thawing, using a sterile surgical gauze.
  Figure 2

Confirm that the VISTASEAL pre-filled syringes are completely thawed. After thawing, the solutions must be clear to slightly opalescent, colorless to pale yellow and must not be cloudy nor have deposits.
Use VISTASEAL immediately during the surgery and discard any unused contents.

Connection instructions

1. Open the blister and make the VISTASEAL Dual Applicator and two additional Airless Spray Tips available to a second person for transfer to the sterile field. The outside of the blister should not come in contact with the sterile field.
2. Hold the VISTASEAL syringe holder with syringe luer caps pointed upward. See Figure 3.
3. Unscrew and discard the syringe luer cap of both fibrinogen and thrombin syringes. See Figure 3.
  Figure 3
4. Hold the syringe holder with the luers pointed upward. To remove air bubbles from syringes, strike gently the side of the syringe holder one or two times while keeping the syringe holder in an upright position and lightly depress the plunger to eject air. See Figure 4.
  Figure 4
5. Attach the Dual Applicator. See Figure 5.
  NOTE: Do not depress plunger during attachment or prior to intended use because the two biologic components will pre-mix in the Airless Spray Tip, forming a fibrin clot that prevents dispensing. See Figure 6.
  Figure 5
  Figure 6
6. Tighten luer locks and ensure the Dual Applicator is firmly attached. The device is now ready to use.

2.3 Administration

For topical use only.

Apply VISTASEAL using the syringe holder and plunger supplied.

Apply VISTASEAL using the Dual Applicator provided with the product. Applicator tips cleared by the FDA for specific use with the VISTASEAL may also be used. When using the provided Dual Applicator, follow the connection instructions in the above section for Preparation. When using other applicator tips, follow the instructions for use that are provided with the applicator tips.

Before administration of VISTASEAL:

- To prevent tissue adhesion at undesired sites, protect (cover) parts of the body outside the intended application area. [see Dosage and Administration (2.4) ]
- Use standard techniques (e.g., intermittent application of compresses, swabs, use of suction devices) to dry the surface area of the target bleeding site.

Application by spraying

1. Grasp and bend the Dual Applicator to the desired position. Tip will retain its shape.
2. Position the Airless Spray Tip at least 2 cm away from the target tissue. Apply firm even pressure to the plunger to spray the fibrin sealant. Increase distance accordingly to achieve desired coverage of the target area.
3. If expression is stopped for any reason, change the Airless Spray Tip prior to resuming application since a clot may form inside the Airless Spray Tip. To change the Airless Spray Tip, remove the device from the patient and unscrew the used Airless Spray Tip. See Figure 7. Place the used Airless Spray Tip away from the spare Airless Spray Tips. Wipe the end of the applicator using dry or moist sterile surgical gauze. Then, connect a new Airless Spray Tip provided in the package and ensure it is firmly connected before use.
  NOTE: Red indicator will not be visible if Airless Spray Tip is properly connected. See Figure 8.
  NOTE: Do not continue pushing the plunger in an attempt to clear the fibrin clot within the Airless Spray Tip; otherwise the applicator may become unusable.
  NOTE: Do not trim the Dual Applicator to avoid exposing internal wire.
  Figure 7
  Figure 8

Application by dripping

1. Remove the Airless Spray Tip portion of the spray and drip tip by unscrewing the Airless Spray Tip.
  See Figure 7.
2. Grasp and bend the drip tip to the desired position. Tip will retain its shape.
3. During dripping, keep the end of the drip tip as close to the tissue surface as possible without touching the tissue during application.
4. Apply individual drops to the surface area to be treated. To prevent uncontrolled clotting, allow the drops to separate from each other and from the end of the drip tip.
  NOTE: Do not reconnect a used drip tip after it has been removed from the adapter; otherwise a clot may form inside the drip tip and the applicator may become unusable.

2.4 Application precautions

- Before administration of VISTASEAL, protect (cover) parts of the body outside the desired application area to prevent tissue adhesion at undesired sites. [see Dosage and Administration (2.3)]
- Apply VISTASEAL as a thin layer. Excessive clot thickness may negatively interfere with the product’s efficacy and the wound healing process. [see Dosage and Administration (2.1)]
- Only spray VISTASEAL if it is possible to accurately judge the distance from the spray tip to the tissue surface. [see Dosage and Administration (2.3)]
- No clinical data are available to support the use of this product in neurosurgery or application through a flexible endoscope for treatment of bleeding.

3 DOSAGE FORMS AND STRENGTHS

VISTASEAL is supplied as a kit consisting of two separate packages:

- A package containing one syringe each of human fibrinogen 80 mg/mL (component 1) and human thrombin 500 IU/mL (component 2) sterile frozen solutions which are assembled on a syringe holder.
- A package containing a Dual Applicator with two additional Airless Spray Tips.

The available package sizes of VISTASEAL are shown in Table 3.

Table 3. VISTASEAL Package Sizes
Package size (Total volume) | Human fibrinogen | Human thrombin
2 mL | 1 mL | 1 mL
4 mL | 2 mL | 2 mL
6 mL | 3 mL | 3 mL
10 mL | 5 mL | 5 mL

4 CONTRAINDICATIONS

- Do not inject directly into the circulatory system. [see Warnings and Precautions (5.1)]
- Do not use for the treatment of severe or brisk arterial bleeding. In these situations, blood flow will wash away VISTASEAL and prevent hemostasis.
- Do not use VISTASEAL in patients known to have anaphylactic or severe systemic hypersensitivity reactions to the administration of human blood products. [see Warnings and Precautions (5.2)]
- Do not use VISTASEAL for spraying unless the minimum recommended distance from the applicator tip to the bleeding site can be achieved. [see Dosage and Administration (2.3)]

5 WARNINGS AND PRECAUTIONS

5.1 Thrombosis

Life-threatening thromboembolic complications may occur if VISTASEAL is administered intravascularly.

5.2 Hypersensitivity

Allergic-type hypersensitivity reactions are possible. Signs of hypersensitivity reactions include hives, generalized urticaria, tightness of the chest, wheezing, hypotension, and anaphylaxis. If these symptoms occur, discontinue the administration of VISTASEAL immediately. Treat the reaction accordingly.

5.3 Transmissible Infectious Agents

Because VISTASEAL is made from human plasma, it may carry a risk of transmitting infectious agents, e.g., viruses, the variant Creutzfeldt-Jakob disease (vCJD) agent and theoretically, the Creutzfeldt-Jakob (CJD) agent. This also applies to unknown or emerging viruses and other pathogens. All suspected infections related to this product should be reported by the physician or other healthcare provider to Grifols Therapeutics LLC at 1-800-520-2807. The physician should discuss the risks and benefits of the use of VISTASEAL with the patient. [see Patient Counseling Information (17)]

6 ADVERSE REACTIONS

6.1 Clinical Trials Experience

Because clinical trials are conducted under widely varying conditions, adverse reaction rates observed in the clinical trials of a drug cannot be directly compared to rates in the clinical trials of another drug and may not reflect the rates observed in clinical practice.
The safety data described in this section reflect exposure to VISTASEAL in four clinical studies. A total of 591 patients (489 adults and 102 pediatric) received VISTASEAL for vascular (Study 1), parenchymal (Study 2 and Study 4), or soft tissue (Study 3 and Study 4) surgery. [see Clinical Studies (14)]
The most frequently occurring adverse reactions are shown in Tables below.
In the VISTASEAL group in these 4 trials, 11% of trial patients experienced one or more adverse reactions, and 7% of control patients experienced one or more adverse reactions.

Table 4. Adverse Reactions Occurring in >1% of Patients in Study 1, 2, and 3 and Study 4 (Combined)
Preferred Term | N = 591 n (%)
Procedural pain | 11 (2)
Nausea | 6 (1)

Table 5. Adverse Reactions Occurring in >1% of Patients in Study 1
Preferred Term | N = 168 n (%)
Procedural pain | 4 (2)
Nausea | 2 (1)
Pyrexia (fever) | 2 (1)
Vascular graft complication | 2 (1)
Parvovirus B19 test positive | 2 (1)
Urinary retention (Unable to empty the bladder completely) | 2 (1)

Table 6. Adverse Reactions Occurring in >1% of Patients in Study 2
Preferred Term | N = 163 n (%)
Postprocedural bile leak | 2 (1)
Procedural pain | 2 (1)
Pulmonary embolism (Blood clot in the lungs) | 2 (1)
Deep vein thrombosis (Blood clot that forms in a vein deep) | 2 (1)

Table 7. Adverse Reactions Occurring in >1% of Patients in Study 3
Preferred Term | N = 169 n (%)
Nausea | 4 (2)
Procedural pain | 4 (2)
Pruritus (Itching) | 4 (2)
Anemia (Low red blood cells) | 2 (1)
Leukocytosis (Increased white blood cells) | 2 (1)
Ileus (Decreased or absent movement of the stomach or intestine) | 2 (1)
Alanine aminotransferase increased | 2 (1)
Aspartate aminotransferase increased | 2 (1)
Hypocalcemia (Low serum calcium) | 2 (1)
Hypokalemia (Low serum potassium) | 2 (1)
Hyponatremia (Low serum sodium) | 2 (1)
Prothrombin time prolonged (Increased bleeding time) | 2 (1)
Headache | 2 (1)
Insomnia | 2 (1)
Hypertension | 2 (1)

Additionally, in the pediatric clinical study (Study 4) conducted to assess safety and efficacy of VISTASEAL compared to EVICEL (human fibrin sealant), one adverse reaction (procedural pain) occurred in one patient (1%) who received VISTASEAL. [see Pediatric Use (8.4) and Clinical Studies [14]]

6.2 Postmarketing Experience

The following adverse reactions have been identified during post-approval use of VISTASEAL. Because these reactions are reported voluntarily from a population of uncertain size, it is not always possible to reliably estimate their frequency or establish a causal relationship to drug exposure.
General disorders and administration site conditions: adhesions

8 USE IN SPECIFIC POPULATIONS

8.1 Pregnancy

Risk Summary
There are no available data with VISTASEAL use in pregnant women. Animal reproduction studies have not been performed with VISTASEAL. It is unknown whether VISTASEAL can cause fetal harm when administered to a pregnant woman or can affect reproductive capacity. In the U.S. general population, the estimated background risk of major birth defect and miscarriage in clinically recognized pregnancies is 2-4% and 15-20%, respectively.

8.2 Lactation

Risk Summary
There is no information regarding the presence of VISTASEAL in human milk, the effects on the breastfed infant, or the effects on milk production. The developmental and health benefits of breastfeeding should be considered along with the mother’s clinical need for VISTASEAL and any potential adverse effects on the breastfed infant from VISTASEAL or from the underlying maternal condition.

8.4 Pediatric Use

The safety and effectiveness of VISTASEAL have been established in pediatric patients as an adjunct to hemostasis during surgery. The use of VISTASEAL for this indication is supported by evidence from adequate and well-controlled studies for assessment of safety and efficacy in pediatric patients in the following age groups: 4 neonates (aged ≤ 27 days), 24 infants (aged ≥ 28 days to 23 months), 39 children (aged 2 years to < 12 years) and 39 adolescents aged 12 years to < 18 years of age. [see Adverse Reactions (6.1) and Clinical Studies (14)]

8.5 Geriatric Use

Clinical trials included 172 subjects aged 65 years or older treated with VISTASEAL. No differences in safety or effectiveness were observed between these subjects and younger patients.

11 DESCRIPTION

VISTASEAL is a two-component fibrin sealant consisting of human fibrinogen (component 1) and human thrombin with calcium chloride (component 2) sterile solutions filled in syringes which are assembled in a syringe holder.

VISTASEAL is supplied as frozen solutions. After thawing, the human fibrinogen and human thrombin solutions are clear or slightly opalescent and colorless or pale yellow. VISTASEAL does not contain any preservatives.

Fibrinogen

Component 1 is a sterile solution, pH 6.5 – 8.0, which contains concentrated human fibrinogen and excipients. Fibrinogen is a protein from human blood that forms a clot when combined with thrombin. The composition of the human fibrinogen solution is as follows:
Active ingredient: human fibrinogen (80 mg/mL)
Other ingredients: sodium citrate, sodium chloride, arginine, L-isoleucine, L-glutamic acid monosodium and water for injection.

Thrombin

Component 2 is a sterile solution, pH 6.0 – 8.0, which contains purified human thrombin and excipients. Thrombin is a specific protease that activates clotting of the final combined product and converts fibrinogen to fibrin. The composition of the human thrombin solution is as follows:
Active ingredient: human thrombin (500 IU/mL)
Other ingredients: calcium chloride, human albumin, sodium chloride, glycine and water for injection.

The starting material for the production of both fibrinogen and thrombin components of VISTASEAL is pooled human Source Plasma obtained from FDA-licensed plasma collection centers in the United States. Cohn’s plasma fractionation method is used to obtain Fraction I, which is the starting material for the production of fibrinogen, and the prothrombin complex isolated from supernatant of Fraction I, which is the starting material for the production of thrombin. The purification process of fibrinogen includes solvent/detergent treatment, three glycine precipitation steps, and double nanofiltration using 35-nm and 20-nm filters. The purification process of thrombin includes solvent/detergent treatment, ion exchange chromatography, and double nanofiltration through 15-nm filters. After nanofiltration, the fibrinogen and thrombin solutions are formulated, sterile filtered, aseptically filled in syringes, packaged, sterilized, and frozen.

Viral safety
Individual plasma donations used in the manufacture of VISTASEAL are collected in FDA-licensed plasma donation centers in the U.S. and are tested for viral markers in compliance with the U.S. regulatory requirements. In addition, mini-pools of plasma units are tested as an in-process control for hepatitis A virus (HAV) and parvovirus B19 (B19V) using validated nucleic acid testing (NAT) methods. All the tests must be non-reactive (negative) except for B19V, for which the limit in plasma manufacturing pools does not exceed a titer of 10^4 IU/mL. The manufacturing plasma pool is also tested with NAT for HBV, HCV, and HIV, and all the tests must be non‑reactive (negative).

The manufacturing processes for fibrinogen and thrombin include processing steps which are designed to reduce the risk of viral transmission. Both components have two discrete steps with viral clearance capacity, namely solvent/detergent treatment (with 1.0% (v/v) Tween 80/0.30% (v/v) tri-n-butyl phosphate (TNBP) for 6.0 – 6.5 hours at 27.0 ± 1.5 ºC for fibrinogen or 25 ± 1 ºC for thrombin), validated to inactivate enveloped viruses, and a nanofiltration step validated to remove non-enveloped and enveloped viruses (35-nm and 20-nm filters for fibrinogen and two 15-nm filters for thrombin). Additionally, the glycine precipitation steps contribute to the overall safety of the product in the purification process of human fibrinogen. The Fraction I precipitation and ion-exchange chromatography steps contribute to the overall safety of the product in the purification process of human thrombin.

The viral clearance capacity of these virus inactivation/removal procedures has been validated in small-scale in vitro studies using relevant and model viruses with a range of physico-chemical characteristics. The results of viral clearance validation studies are summarized in Tables 8 and 9:

Table 8. Global Virus Reduction Factors (Log10) for Human Fibrinogen
Manufacturing step | Virus reduction factor (log10)*
Manufacturing step | Enveloped viruses |  |  |  | Non-enveloped viruses
Manufacturing step | HIV-1 | PRV | WNV | BVDV | HAV | PPV
S/D treatment | ≥ 5.33 | ≥ 6.80 | ≥ 5.20 | ≥ 5.60 | n.a. | n.a.
Glycine precipitations | n.d. | n.d. | n.d. | n.d. | 5.21 | 2.09
Nanofiltration 35 nm and 20 nm | ≥ 5.57 | ≥ 6.09 | ≥ 4.51 | ≥ 4.53 | 5.22 | 4.37
Global virus reduction factor (log10) | ≥ 10.90 | ≥ 12.89 | ≥ 9.71 | ≥ 10.13 | 10.43 | 6.46

Table 9. Global Virus Reduction Factors (Log10) for Human Thrombin
Manufacturing step | Virus reduction factor (log10) [Reduction factor below 1 log10 is not considered in calculating the global virus reduction; n.d.: Not done; n.a.: Not applicable; BVDV: bovine viral diarrhea virus, model for HCV; WNV: West Nile virus; PRV: pseudorabies virus, model for large enveloped DNA viruses; PPV: porcine parvovirus, model for B19V]
Manufacturing step | Enveloped viruses |  |  |  | Non-enveloped viruses
Manufacturing step | HIV-1 | PRV | WNV | BVDV | HAV | PPV
Fraction I precipitation | < 1.0 | 2.13 | 2.78 | 1.34 | 1.18 | < 1.0
S/D treatment | ≥ 5.52 | ≥ 5.85 | ≥ 5.94 | ≥ 5.09 | n.a. | n.a.
SP-Sepharose XL chromatography | n.d. | n.d. | n.d. | n.d. | 4.61 | 3.97
Double nanofiltration 15 nm | ≥ 4.03 | ≥ 5.95 | ≥ 5.42 | ≥ 4.93 | 6.56 | 6.14
Global virus reduction factor (log10) | ≥ 9.55 | ≥ 13.93 | ≥ 14.14 | ≥ 11.36 | 12.35 | 10.11

12 CLINICAL PHARMACOLOGY

12.1 Mechanism of Action

VISTASEAL contains human fibrinogen and human thrombin. When applied onto the wound site and mixed, these biological components generate a cross-linked fibrin clot in a process that recreates the last stage of the human blood coagulation system. Fibrinogen is converted into fibrin monomers and fibrinopeptides by thrombin. The fibrin monomers aggregate and form a fibrin clot which stops the bleeding. Factor XIIIa, which is activated from factor XIII by thrombin, crosslinks fibrin. Calcium ions are required for both the conversion of fibrinogen and the crosslinking of fibrin.

12.2 Pharmacodynamics

There are no relevant pharmacodynamic data on VISTASEAL.

12.3 Pharmacokinetics

VISTASEAL is metabolized in the same way as endogenous fibrin by fibrinolysis and phagocytosis. No pharmacokinetic studies were conducted for VISTASEAL.

13 NONCLINICAL TOXICOLOGY

13.1 Carcinogenicity, Mutagenesis, Impairment of Fertility

No animal studies were conducted to evaluate the carcinogenic or mutagenic effect of VISTASEAL or its effects on fertility.

14 CLINICAL STUDIES

The effectiveness of VISTASEAL was demonstrated in four clinical studies in patients undergoing vascular (Study 1), parenchymal (Study 2 and Study 4), or soft tissue (Study 3 and Study 4) surgery. The details of the studies are described below.
Study 1 (Vascular surgery)
A prospective, randomized, controlled clinical study was performed to evaluate the safety and efficacy of VISTASEAL as adjunct to hemostasis in vascular surgery. Patients underwent vascular surgical procedures utilizing polytetrafluoroethylene graft material on proximal end-to-side arterial anastomosis or upper extremity vascular access arterial anastomosis. The clinical trial was conducted with VISTASEAL using a Fibrijet® applicator.
The primary efficacy outcome was to demonstrate superiority of VISTASEAL compared to manual compression (control) in achieving hemostasis by 4 minutes.
The study enrolled 166 patients with a median age of 64.0 years for VISTASEAL and 61.0 years for control (overall range across groups 22 to 84 years). The population characteristics included 65% Male, 90.4% White, 8.4% Black or African American, 1.2% Asian, 3.0% Hispanic or Latino patients.
VISTASEAL was shown to be superior to the control group (manual compression) when comparing the proportion of patients in each group who achieved hemostasis by 4 minutes (Table 10). Superiority was also established at 10 minutes. The median time to hemostasis was significantly shorter (p‑value <0.001) in the VISTASEAL group (4.0 minutes) compared to the control group (≥10.0 minutes).
The efficacy results are summarized in Table-10 below.

Table 10. Efficacy Results in Study 1 (ITT Population) [Intent-to-treat (ITT) population: includes all patients randomized to VISTASEAL or control.]
Efficacy endpoints | VISTASEAL N=109 n (%) | Control N=57 n (%) | Ratio of -proportions [The ratio of proportion of patients meeting the efficacy endpoint in the two treatment groups (VISTASEAL relative to control).] (95% CI) | P-value
Hemostasis by 4 minutes | 83 (76.1) | 13 (22.8) | 3.3 (2.0, 5.4) | <0.001
Hemostasis by 10 minutes | 96 (88.1) | 26 (45.6) | 1.9 (1.4, 2.6) | <0.001
CI = confidence interval
Tabulated efficacy results are cumulative results.

Study 2 (Parenchyma surgery)
A prospective, randomized, controlled clinical study was performed to evaluate the safety and efficacy of VISTASEAL as adjunct to hemostasis in parenchyma surgery. Patients underwent liver resections. The clinical trial was conducted with VISTASEAL using a Fibrijet® applicator. The primary efficacy outcome was to demonstrate superiority of VISTASEAL compared to oxidized regenerated cellulose (control) in achieving hemostasis by 4 minutes.
The study enrolled 224 patients with a median age of 61.0 years in each arm (overall range across groups 19 to 84 years). The population characteristics included 54.5% male, 93.3% White, 1.3% Black or African American, 4.5% Asian, 0.4% American Indian or Alaskan Native, 0.4% not specified, 5.4% Hispanic or Latino.
VISTASEAL was shown to be superior to the control group (oxidized regenerated cellulose) in achieving hemostasis by 4 minutes (Table 11). The median time to hemostasis was significantly shorter (p-value <0.001) in the VISTASEAL group (2.0 minutes) compared to the control group (3.0 minutes).

Table 11. Efficacy Results in Study 2 (ITT Population) [Intent-to-treat (ITT) population: includes all patients randomized to VISTASEAL or control.]
Efficacy endpoints | VISTASEAL N = 111 n (%) | Control N = 113 n (%) | Ratio of proportions [The ratio of proportions of patients meeting the efficacy endpoint in the two treatment groups (VISTASEAL relative to control).] (95% CI) | P-value
Hemostasis by 4 minutes | 103 (92.8) | 91 (80.5) | 1.2 (1.0, 1.3) | 0.010
Hemostasis by 2 minutes | 62 (55.9) | 47 (41.6) | 1.3 (1.0, 1.8) | 0.045
CI = confidence interval
Tabulated efficacy results are cumulative results.

Study 3 (Soft tissue surgery)
A prospective, randomized, controlled clinical study was performed to evaluate the safety and efficacy of VISTASEAL as adjunct to hemostasis in soft tissue bleeding during retroperitoneal and pelvic surgical procedures, and during mastopexies and abdominoplasties. The clinical trial was conducted with VISTASEAL using a Fibrijet® applicator.
The primary efficacy outcome was to demonstrate non-inferiority of VISTASEAL compared to oxidized regenerated cellulose (control) in achieving hemostasis by 4 minutes.
The study enrolled 224 patients with the median age of 46.0 years for VISTASEAL and 45.0 years for control (overall range across groups 15 to 85 years). The population characteristics included 22.8% male, 77.7% White, 21% Black or African American, 0.9% Asian, 0.4% American Indian or Alaskan Native, 14.3% Hispanic or Latino patients.
The efficacy outcomes are summarized in Table 12 below.

Table 12. Efficacy results in Study 3 (ITT population) [Intent-to-treat (ITT) population: includes all patients randomized to VISTASEAL.]
Efficacy endpoints | VISTASEAL N = 116 n (%) | Control N = 108 n (%) | Ratio of proportions [The ratio of proportions of patients meeting the efficacy endpoint in the two treatment groups (VISTASEAL relative to control).] (95% CI) | P-value
Hemostasis by 4 minutes | 96 (82.8) | 84 (77.8) | 1.1 (0.9, 1.2) | 0.401
CI = confidence interval.
Tabulated efficacy results are cumulative results.

Study 4 (Pediatric parenchyma surgery and soft tissue surgery)
A prospective, multicenter, randomized, active controlled, single-blind, clinical trial conducted to evaluate the safety and efficacy of VISTASEAL as an adjunct to hemostasis during open parenchyma (hepatic) surgery or soft tissue surgery. The clinical trial was conducted with fibrin sealant (human) using a Fibrijet® applicator and VistaSeal™ Dual Applicator with airless tips.
The primary efficacy outcome was to demonstrate non-inferiority of VISTASEAL compared to EVICEL in achieving hemostasis by 4 minutes.
A total of 178 pediatric patients (6 neonates, 37 infants, 63 children, and 72 adolescents) were randomized and treated with VISTASEAL(n=91) or EVICEL as active control (n=87). Of the 178 patients, 89 underwent parenchyma (hepatic) surgical procedures and 89 had soft tissue surgeries. The population characteristics included 63% male, 94% White, 4% Black or African American, <1% Asian, <1% multiple races, and <1% other race patients.
Exposure to VISTASEAL consisted of a single intraoperative administration. The mean volume of VISTASEAL used per pediatric patient was 4.6 mL ± 2.7 mL.
The efficacy outcomes are summarized in Table 13 below.

Table 13. Efficacy results in Study 4 (mITT population) [Modified intent-to-treat (ITT) population: includes all patients randomized who met intraoperative criteria and were treated with any amount of study product.]
Efficacy endpoints | VISTASEAL N = 91 n (%) | Control N = 87 n (%) | Ratio of proportions [The ratio of proportions of patients meeting the efficacy endpoint in the two treatment groups (VISTASEAL relative to control). If the lower limit of the 95% CI was above the non-inferiority margin 0.8, it could be claimed that VISTASEAL was not inferior to EVICEL.] (95% CI) | P-value
Hemostasis by 4 minutes | 88 (96.7) | 83 (95.4) | 1.01 (0.96, 1.07) | <0.001
CI = confidence interval.
Tabulated efficacy results are cumulative results.

Additional information from the pediatric surgery study is described in Adverse Reactions and Use in Specific Populations Pediatric Use. [see Adverse Reactions (6.1) and Pediatric Use (8.4)]

16 HOW SUPPLIED/STORAGE AND HANDLING

VISTASEAL kit is comprised of two separate packages (blisters). One package includes two pre-filled syringes containing sterile frozen solutions of human fibrinogen (component 1) and human thrombin with calcium chloride (component 2), which are assembled on a syringe holder for single use. The syringe plungers are connected by a plunger link to ensure simultaneous application of the biological components. One Dual Applicator with two additional Airless Spray Tips, in the other package, is co-packaged with the product for application by spraying or dripping. The Airless Spray Tips are radiopaque. See Figure 9.

Figure 9

The available package sizes for VISTASEAL are shown in Table 14.

Table 14. VISTASEAL Package Sizes and NDC numbers
VISTASEAL Package Size |  |  | NDC Numbers
Total Volume | Human fibrinogen | Human thrombin | Carton | Blister label
2 mL | 1 mL | 1 mL | 61953-0011-1 | 61953-0011-2
4 mL | 2 mL | 2 mL | 61953-0012-1 | 61953-0012-2
6 mL | 3 mL | 3 mL | 61953-0013-1 | 61953-0013-2
10 mL | 5 mL | 5 mL | 61953-0014-1 | 61953-0014-2

Storage
Store the frozen kit (VISTASEAL fibrin sealant (human) with VISTASEAL Dual Applicator) in a freezer (at -18 °C [0 ºF] or colder) for up to 2 years. The cold storage condition must not be interrupted until use. Thaw before use. Once thawed, do not refreeze.

After thawing, VISTASEAL can be stored before use for not more than 7 days at 2 - 8 °C [36 - 46 °F] or 24 hours at room temperature (20 - 25 °C [68 - 77 °F]) if it remains sealed in the original packaging (blister). Once the blister is opened, use VISTASEAL immediately during the surgery and discard any unused contents.

Keep the sterilized blister in the outer carton to protect from light.

Do not use after the expiration date printed on the outer carton and container labels. Discard if the package is damaged.

17 PATIENT COUNSELING INFORMATION

Discuss the following with patient receiving VISTASEAL.

- Thrombosis: Instruct patients to immediately report to their physician symptoms of thrombosis or embolism which may include pain and/or swelling of an arm or leg with warmth over the affected area, discoloration of an arm or leg, unexplained shortness of breath, chest pain or discomfort that worsens on deep breathing, unexplained rapid pulse, numbness or weakness on one side of the body. [see Thrombosis (5.1)]
- Hypersensitivity: Inform patient that hypersensitivity reaction may occur with VISTASEAL. Advise patient to seek immediate medical evaluation if any signs and symptoms of hypersensitivity occur such as itching, rash or hives, or breathing problems. [see Warnings and Precautions (5.2)]
- Transmissible Infectious Agents: Inform patients that VISTASEAL is made from human plasma and may carry a risk of transmitting infectious agents (e.g., viruses, the vCJD agent and, theoretically, the CJD agent). Instruct patients to report any symptoms that concern them and might be caused by infections. [see Warnings and Precautions (5.3)]

Manufactured by:
INSTITUTO GRIFOLS, S.A.
BARCELONA - SPAIN
U.S. License No. 1181
Distributed by:
Ethicon, Inc.
1000 Route 202
Raritan, New Jersey 08869
USA • 1-877-ETHICON • +1-513-337-6928
© Ethicon, Inc. 2023

PACKAGE LABEL.PRINCIPAL DISPLAY PANEL

NDC 61953-0011-1
ETHICON
VistaSeal™
Fibrin Sealant (Human)
VISTASEAL™
Frozen solutions
2 mL
ETHICON
Reorder number
VST02
Fibrin Sealant (Human)
VISTASEAL™
Frozen solutions
2 mL
ETHICON
Fibrin Sealant (Human)
VISTASEAL™
Frozen solutions
2 mL
Human Fibrinogen / Human Thrombin - For topical use. Do not inject.
CONTENTS
• 2 pre-filled syringes, each with a sterile frozen solution, assembled in a syringe holder for
single use.
• 1 Dual Applicator with 2 additional Airless Spray Tips.
Component 1: 1 mL of human fibrinogen (80 mg/mL). Other ingredients: Sodium citrate,
sodium chloride, arginine, L-isoleucine, L-glutamic acid monosodium and water for injection.
Component 2: 1 mL of human thrombin (500 IU/mL). Other ingredients: Calcium chloride,
human albumin, sodium chloride, glycine and water for injection.
Contains no preservatives.
Rx only
NDC 61953-0011-1
Fibrin Sealant (Human)
VISTASEAL™
Frozen solutions
2 mL
Distributed by:
Ethicon, Inc.
1000 Route 202
Raritan, New Jersey 08869
USA • 1-877-ETHICON • +1-513-337-6928
© Ethicon, Inc. 2022
pat. www.ethicon.com/patentmarking
Manufactured by:
Instituto Grifols, S.A.
2 Can Guasch St. Polígono Levante
08150 Parets del Vallès
Barcelona - SPAIN
U.S. License No. 1181
Store in a freezer (-18 °C [0 °F] or colder). The cold storage chain must not be interrupted until use.
Keep the sterilized blister in the outer carton in order to protect from light.
Thaw for use. Do not refreeze once thawed. After thawing, the kit can be stored before use for not
more than 7 days at 2 - 8 °C [36 - 46 °F] or 24 hours at room temperature (20 - 25 °C [68 - 77 °F]) if
it remains sealed in the original packaging. Once packaging is opened, use product immediately.
For usage instructions and precautions, see enclosed package insert.
Discard any unused contents and administration devices after use.
Reorder number
VST02
Fibrin Sealant (Human)
VISTASEAL™
Frozen solutions
2 mL
ETHICON
GTIN: 00361953001118
SN: XXXXXXXXXXXXXXXX
Lot XXXXXXXXXX
EXP DD-MMM-YYYY
P-1

VistaSeal™
Fibrinogen
80 mg/mL
1 mL
Lot
EXP
3062006

VistaSeal™
Thrombin
500 IU/mL
1 mL
Lot
EXP
3062007

VistaSeal™ 2mL
Lot
EXP
Thawed Exp:
3055495

Fibrin Sealant (Human)
VistaSeal™
Frozen solutions
NDC 61953-0011-2
2 mL
Rx only
Human Fibrinogen / Human Thrombin - For topical use. Do not inject.
CONTENTS
2 pre-filled syringes, each with a sterile frozen solution, assembled in a syringe holder for single use.
Component 1: 1 mL of human fibrinogen (80 mg/mL). Other ingredients: Sodium citrate, sodium chloride,
arginine, L-isoleucine, L-glutamic acid monosodium and water for injection.
Component 2: 1 mL of human thrombin (500 IU/mL). Other ingredients: Calcium chloride,
human albumin, sodium chloride, glycine and water for injection.
Contains no preservatives. Store in a freezer (-18 °C [0 °F] or colder). Thaw for use.
Do not refreeze once thawed. For usage instructions and precautions, see enclosed package insert.
ETHICON
LOT
EXP
Manufactured by: Instituto Grifols, S.A.
Barcelona - SPAIN. U.S. License No. 1181
3063058